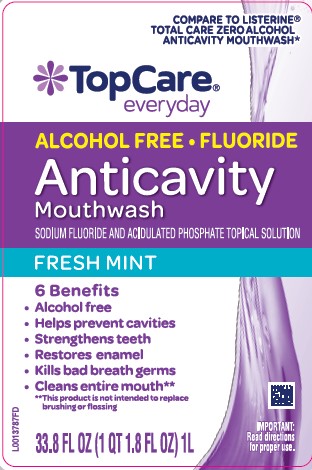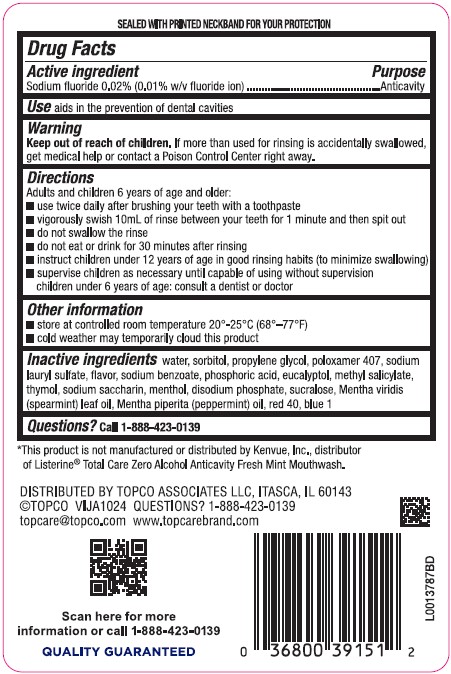 DRUG LABEL: Anticavity
NDC: 36800-971 | Form: RINSE
Manufacturer: Topco Associates LLC
Category: otc | Type: HUMAN OTC DRUG LABEL
Date: 20260213

ACTIVE INGREDIENTS: SODIUM FLUORIDE 0.1 mg/1 mL
INACTIVE INGREDIENTS: WATER; SORBITOL; PROPYLENE GLYCOL; POLOXAMER 407; SODIUM LAURYL SULFATE; SODIUM BENZOATE; PHOSPHORIC ACID; EUCALYPTOL; METHYL SALICYLATE; THYMOL; SACCHARIN SODIUM; MENTHOL; SODIUM PHOSPHATE, DIBASIC, ANHYDROUS; SUCRALOSE; SPEARMINT OIL; PEPPERMINT OIL; FD&C RED NO. 40; FD&C BLUE NO. 1

Top Care 971.001/971AB
Burn-Free Fluoride Anti-Cavity Mouthwash

Tamper Evident Statement

SEALED WITH PRINTED NECKBAND FOR YOUR PROTECTION

Active Ingredient

Sodium fluoride 0.02% (0.01% w/v fluoride ion)

Purpose

Anticavity

Use

aids in the prevention of dental cavities

Warning

for this product

Keep out of Reach of Children

If more than used for rinsing is accidentally swallowed, get medical help or contact a Poison Control Center right away.

Directions

Adults and children 6 years of age and older:

- use twice daily after brushing your teeth with a toothpaste
- vigorously swish 10 mL of rinse between your teeth for 1 miute and then spit out.
- do not swallow the rinse
- do not eat or drink for 30 minutes after rinsing
- instruct children under 12 years of age in good rinsing habits (to minimize swallowing)
- supervise children as necessary until capable of using without supervision
- children under 6 years of age: consult a dentist or doctor

Other information

- store at room temperature 20⁰ - 25⁰ C (68⁰ - 77⁰ F)
- cold weather may temporarily cloud this product

Inactive ingredients

water, sorbitol, propylene glycol, poloxamer 407, sodium lauryl sulfate, flavor, sodium benzoate, phosphoric acid, eucalyptol, methyl salicylate, thymol, sodium saccharin, menthol, disodium phosphate, sucralose, Mentha viridis (spearmint) leaf oil, Mentha piperita (peppermint) oil, red 40, blue 1

Disclaimer

*This product is not manufactured or distributed by Kenvue, Inc., distributor of Listerine®Total Care Zero Alcohol Anticavity Fresh Mint Mouthwash.

Adverse reactions section

DISTRIBUTED BY TOPCO ASOCIATES LLC, ITASCA, IL 60143

©TOPCO VIJA1024 QUESTIONS? 1-888-423-0139

topcare@topco.com www.topcarebrand.com

Scan here for more information or call 1-888-423-0139

QUALITY GUARANTEED

principal display panel

COMPARE TO LISTERINE®TOTAL CARE ZERO ALCOHOL ANTICAVITY MOUTHWASH*

Top Care®

everyday

ALCOHOL FREE • FLUORIDE

Anticavity

Mouthwash

SODIUM FLUORIDE AND ACIDULATED PHOSPHATE TOPICAL SOLUTION

FRESH MINT

6 Benefits

- Alcohol free
- Helps prevent cavities
- Strengthens teeth
- Restores enamel
- Kills bad breath germs
- Cleans entire mouth**

**This product is not intended to replace brushing or flossing

IMPORTANT: Read direction for proper use.

33.8 FL OZ (1 QT 1.8 FL OZ) 1 L